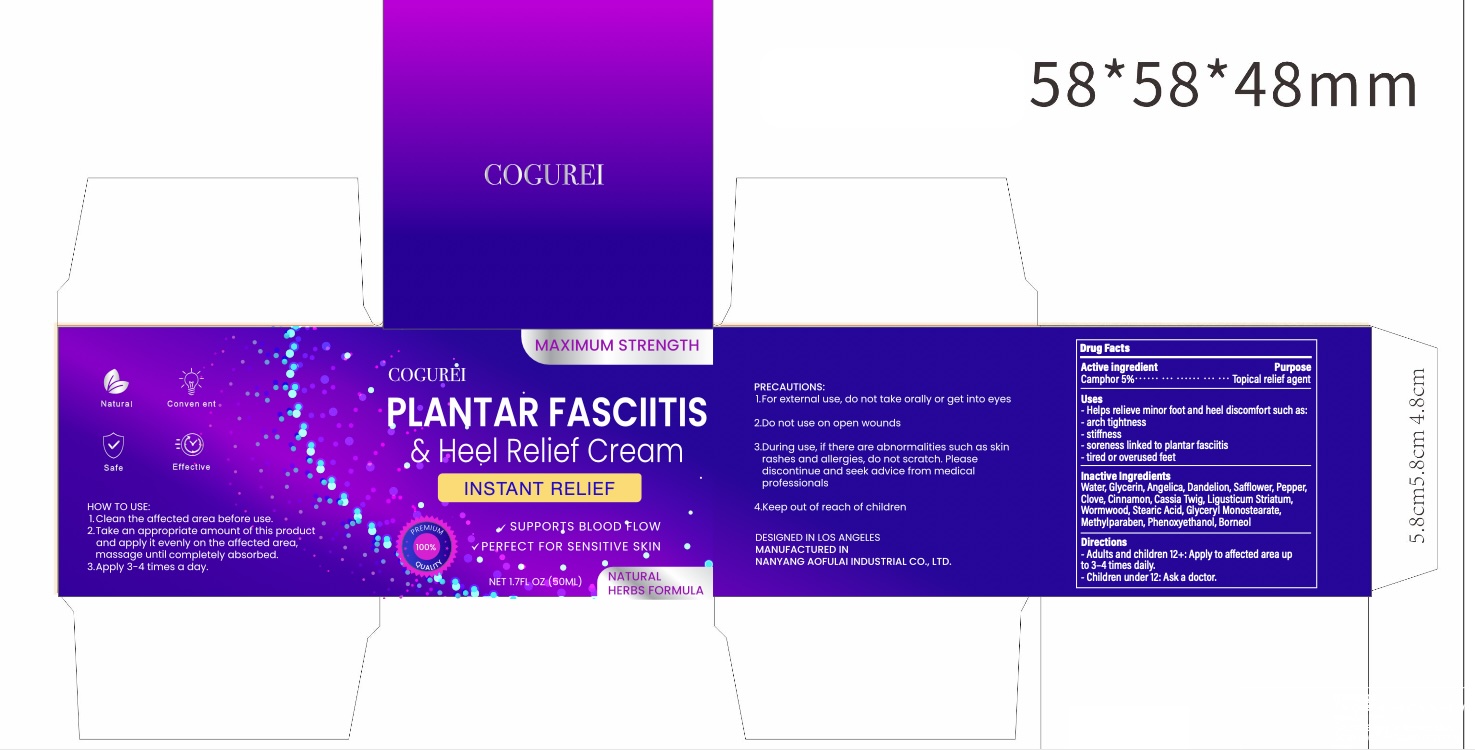 DRUG LABEL: Plantar Fasciitis Cream
NDC: 85849-012 | Form: CREAM
Manufacturer: SOLALIA LLC
Category: otc | Type: HUMAN OTC DRUG LABEL
Date: 20250627

ACTIVE INGREDIENTS: CAMPHOR, (-)- 50 mg/1 mL
INACTIVE INGREDIENTS: WATER; ANGELICA SINENSIS ROOT; TARAXACUM OFFICINALE; SAFFLOWER; CLOVE; CINNAMOMUM CASSIA TWIG; WORMWOOD; STEARIC ACID; GLYCERYL MONOSTEARATE; METHYLPARABEN; PHENOXYETHANOL; BORNEOL; GLYCERIN; LIGUSTICUM WALLICHII ROOT; BLACK PEPPER; CINNAMON

Initial Drug Listing - Plantar Fasciitis Cream

ACTIVE INGREDIENT

Camphor 5%

PURPOSE

Topical Analgesic

INDICATIONS AND USAGE

- helps relieve minor foot and heel discomfort such as: arch tightness, stiffness, soreness linked to plantar fasciitis, ired or overused feet

WARNINGS

For external use, do not take orally or get into eyes

Do not use on open wounds.

WHEN USING

- if there are abnormalities such as skin rashes and allergies, do not scratch.
- Avoid contact with eyes and mucous membranes

STOP USE

If you experience an allergic reaction, discontinue use and consult a physician

KEEP OUT OF REACH OF CHILDREN

If swallowed, get medical help or contact a Poison Control Center right away.

DOSAGE AND ADMINISTRATION

- Clean the affected area before use.
- Take an appropriate amount of this product and apply it evenly on the affected area, massage until completely absorbed.
- Adults and children 12+, apply to affected area up to 3-4 times daily.
- Children under 12, ask a doctor.

OTHER SAFETY INFORMATION

Store tightly closed in a dry place at controlled room temperature between 59°-86° F (15°-30° C).

INACTIVE INGREDIENT

Water, Glycerin, Angelica Sinensis Root, Taraxacum Officinale, Safflower, Black Pepper, Clove, Cinnamon, Cinnamomum Cassia Twig, Ligusticum Wallichii Root, Wormwood, Stearic Acid, Glyceryl Monostearate, Methylparaben, Phenoxyethanol, Borneol

QUESTIONS

please contact us at: scogurei@gmail.com